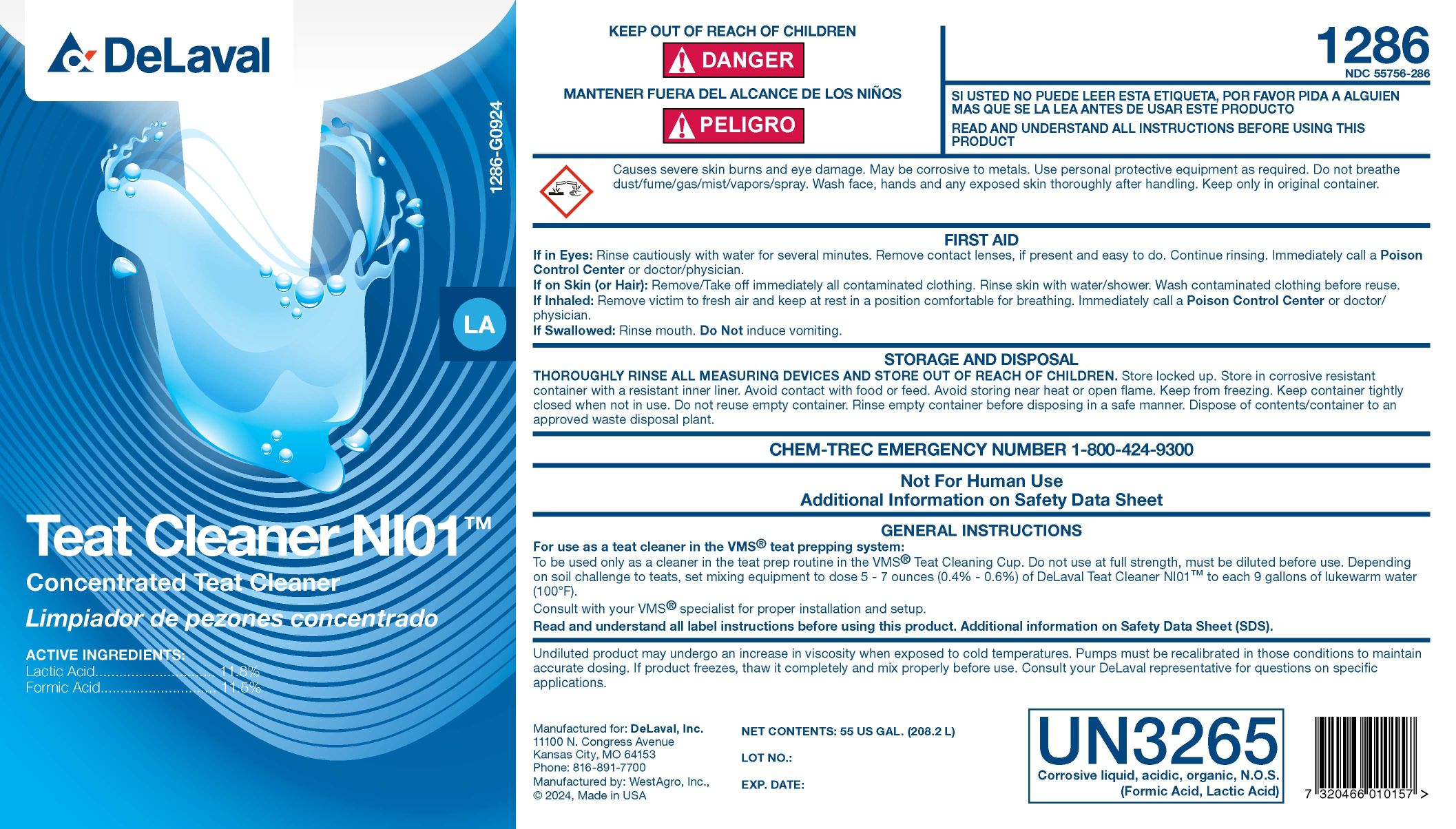 DRUG LABEL: Teat Cleaner NI01
NDC: 55756-286 | Form: SOLUTION, CONCENTRATE
Manufacturer: Delaval
Category: animal | Type: OTC ANIMAL DRUG LABEL
Date: 20241217

ACTIVE INGREDIENTS: LACTIC ACID 118 g/1 L; FORMIC ACID 115 g/1 L
INACTIVE INGREDIENTS: SODIUM C14-16 OLEFIN SULFONATE; SODIUM LAURETH-3 SULFATE; DOCUSATE SODIUM; FD&C BLUE NO. 1; C9-11 PARETH-8

Teat Cleaner NI01

INDICATIONS AND USAGE

Concentrated Teat Cleaner

ACTIVE INGREDIENTS:

Lactic Acid ............................... 11.8%

Formic Acid .............................. 11.5%

KEEP OUT OF REACH OF CHILDREN

! DANGER

MANTENER FUERA DEL ALCANCE DE LOSS NINOS

! PELIGRO

1286

NDC 55756-286

GENERAL PRECAUTIONS

SI USTED NO PEUDE LEER ESTA ETIQUETA, POR FAVOR PIDA A ALGUIEN MAS QUE SE LA LEA ANTES DE USAR ESTE PRODUCTO

READ AND UNDERSTAND ALL INSTRUCTIONS BEFORE USING THIS PRODUCT

WARNINGS

Causes severe skin burns and eye damage. May be corrosive to metals. Use personal protective equipment as required. Do not breathe dust/fume/gas/mist/vapors/spray. Wash face, hands and any exposed skin thoroughly after handling. Keep only in original container.

FIRST AID

If in Eyes: Rinse cautiously with water for several minutes. Remove contact lenses, if present and easy to do. Continue rinsing. Immediately call a Poison Control Center or doctor/physician.

If on Skin (or Hair): Remove/Take off immediately all contaminated clothing. Rinse skin with water/shower. Wash contaminated clothing before reuse.

If Inhaled: Remove victim to fresh air and keep at rest in a position comfortable for breathing. Immediately call a Poison Control Center or doctor/physician.

If Swallowed: Rinse mouth. Do Not induce vomiting.

STORAGE AND DISPOSAL

THOROUGHLY RINSE ALL MEASURING DEVICES AND STORE OUT OF REACH OF CHILDREN.

Store locked up. Store in corrosive resistant container with a resistant inner lining. Avoid contact with food or feed. Avoid storing near heat or open flame. Keep from freezing. Keep container tightly closed when not in use. Do not reuse empty container. Rinse empty container before disposing in a safe manner. Dispose of contents/container to an approved waste disposal plant.

CHEM-TREC EMERGENCY NUMBER 1-800-424-9300

GENERAL PRECAUTIONS

Not For Human Use

Additional Information on Safety Data Sheet

GENERAL INSTRUCTIONS

For use as a teat cleaner in the VMS® teat prepping system:

To be used only as a cleaner in the teat prep routine in the VMS® Teat Cleaning Cup. Do not use at full strength, must be diluted before use. Depending on soil challenge to teats, set mixing equipment to dose 5 - 7 ounces (0.4% - 0.6%) of DeLaval Teat Cleaner NI01™ to each 9 gallons of lukewarm water (100º F).

Consult with your VMS® specialist for proper installation and setup.

Read and understand all label instructions before using this product. Additional information on Safety DataSheet (SDS).

WARNINGS AND PRECAUTIONS

Undiluted product may undergo an increase in viscosity when exposed to cold temperatures. Pumps must be recalibrated in those conditions to maintain accurate dosing. If product freezes, thaw it completely and mix properly before use. Consult your DeLaval representative for questions on specific applications.

SAFE HANDLING WARNING

UN3265

Corrosive liquid, acidic, organic, N.O.S. (Formic Acid, Lactic Acid)

Manufactured for: DeLaval, Inc.
11100 N. Congress Avenue
Kansas City, MO 64153
Phone: 816-891-7700
Manufactured by: WestAgro, Inc.
©2024, Made in USA

NET CONTENTS:

LOT NO.:

EXP. DATE:

PACKAGE LABEL

Add image transcription here...